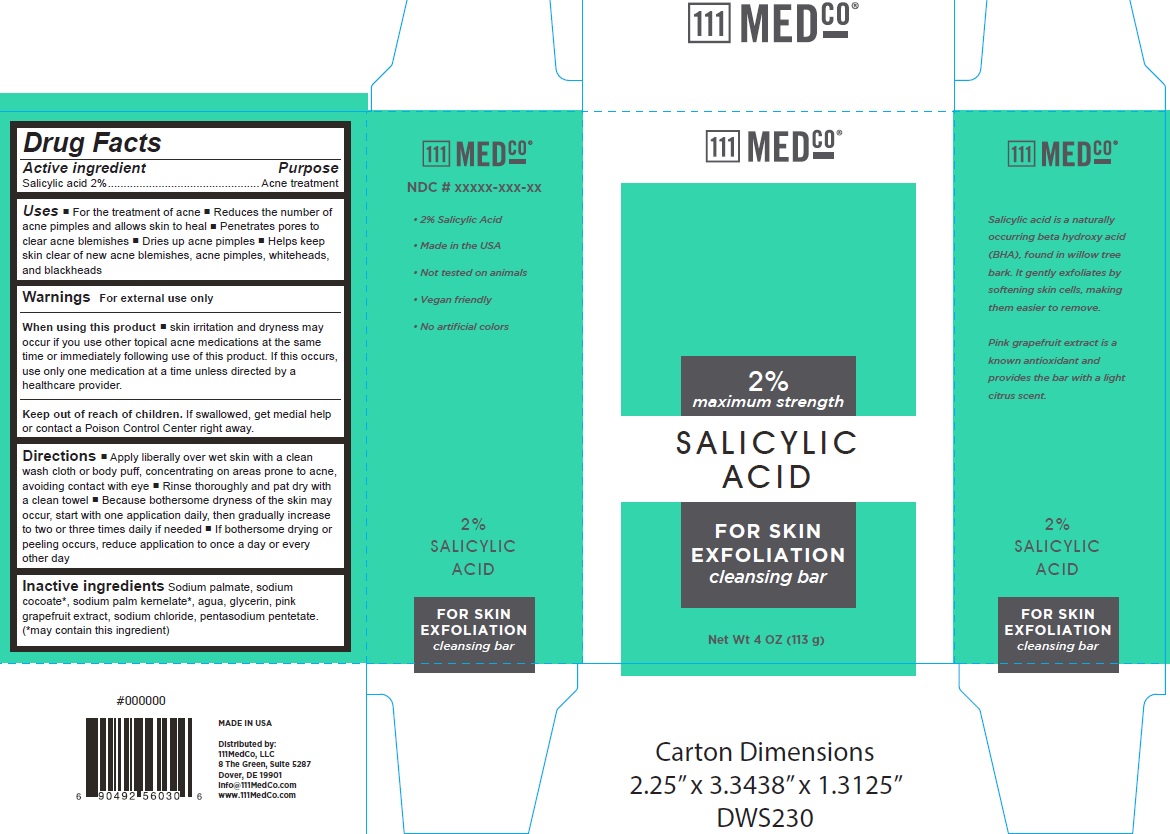 DRUG LABEL: 111MedCo 2% Salicylic Acid Cleansing Bar
NDC: 72811-000 | Form: SOAP
Manufacturer: 111MedCo LLC
Category: otc | Type: HUMAN OTC DRUG LABEL
Date: 20231212

ACTIVE INGREDIENTS: SALICYLIC ACID 20 mg/1 g
INACTIVE INGREDIENTS: SODIUM PALMATE; SODIUM COCOATE; SODIUM PALM KERNELATE; GLYCERIN; SODIUM CHLORIDE; PENTASODIUM PENTETATE

111MedCo 2% Salicylic Acid Cleansing Bar

Active ingredient

Salicylic acid 2%

Purpose

Acne treatment

Uses

- For the treatment of acne
- Reduces the number of acne pimples and allows skin to heal
- Penetrates pores to clear acne blemishes
- Dries up acne pimples
- Helps keep skin clear of new acne blemishes, acne pimples, whiteheads, and blackheads

Warnings

For external use only

When using this product

skin irritation and dryness may occur if you use other topical acne medications at the same time or immediately following use of this product. If this occurs, use only one medication at a time unless directed by a healthcare provider.

Keep out of reach of children.

If swallowed, get medial help or contact a Poison Control Center right away.

Directions

- Apply liberally over wet skin with a clean wash cloth or body puff, concentrating on areas prone to acne, avoiding contact with eye Rinse thoroughly and pat dry with a clean towel
- Because bothersome dryness of the skin may occur, start with one application daily, then gradually increase to two or three times daily if needed
- If bothersome drying or peeling occurs, reduce application to once a day or every other day

Inactive ingredients

Sodium palmate, sodium cocoate*, sodium palm kernelate*, agua, glycerin, pink grapefruit extract, sodium chloride, pentasodium pentetate. (*may contain this ingredient)